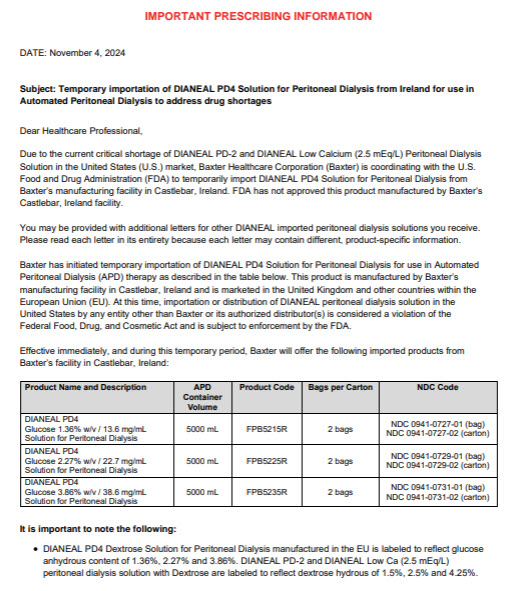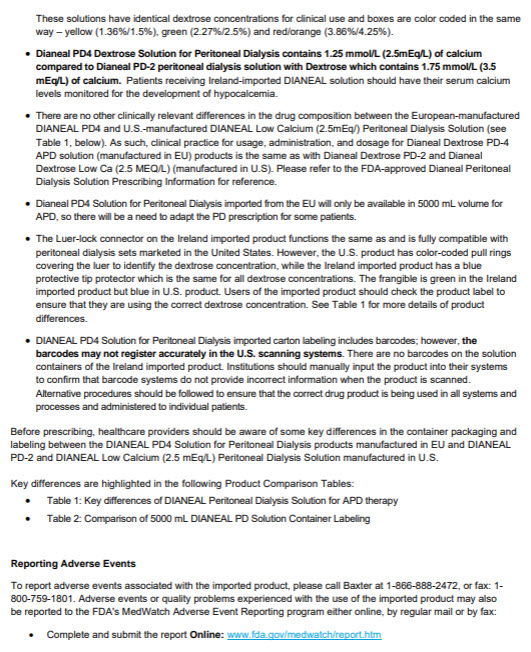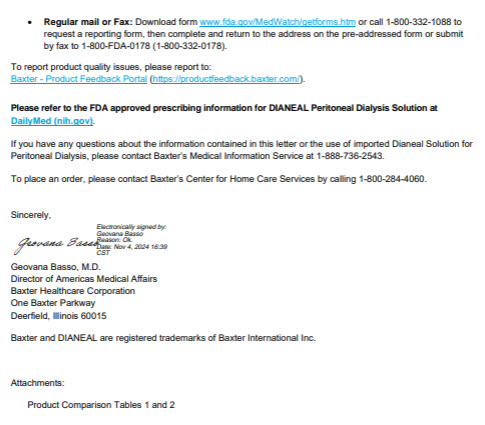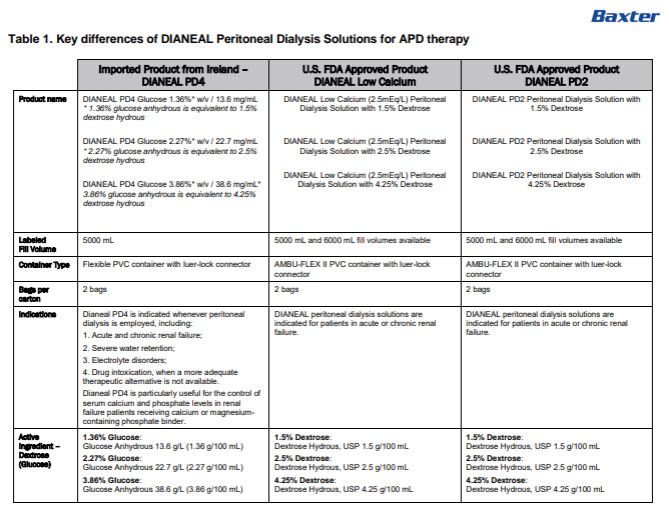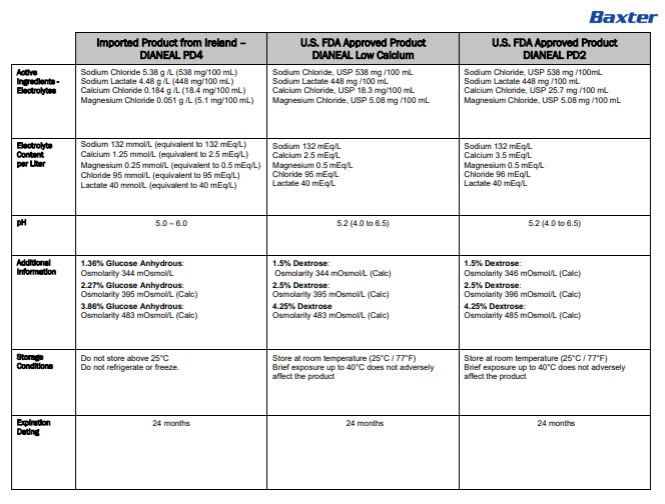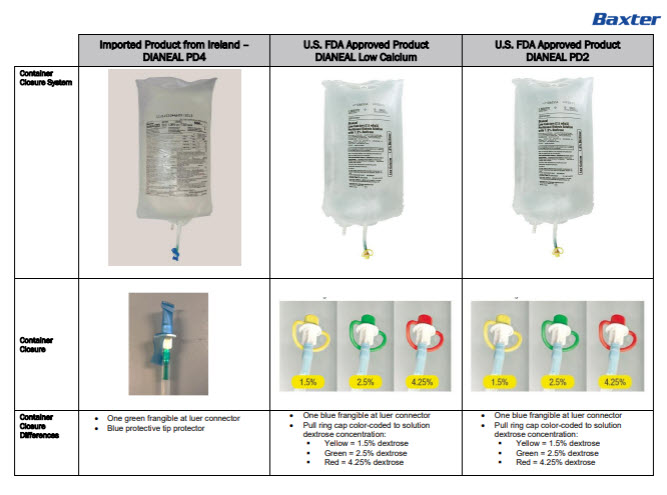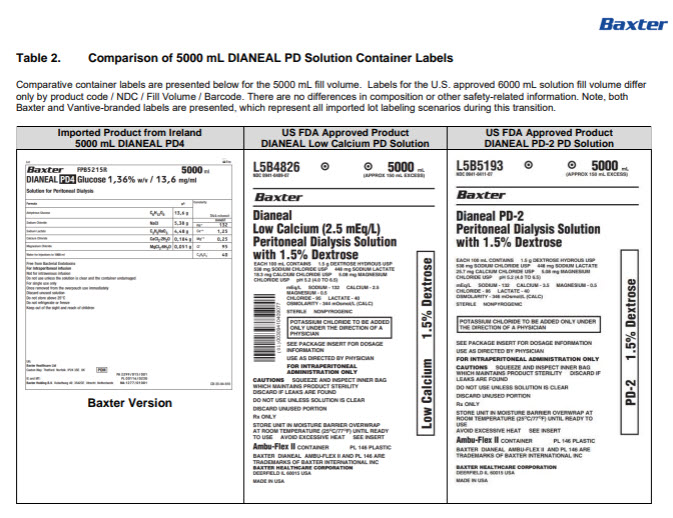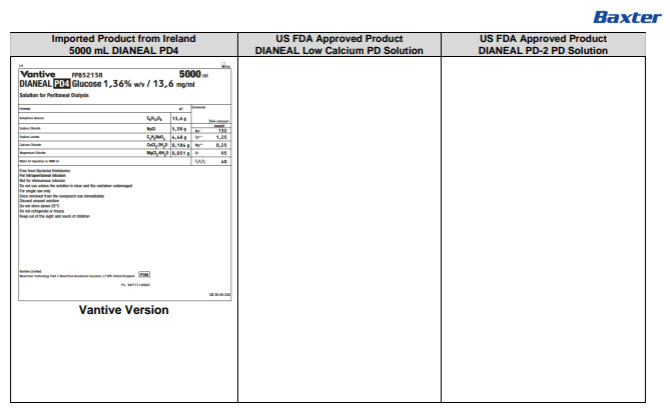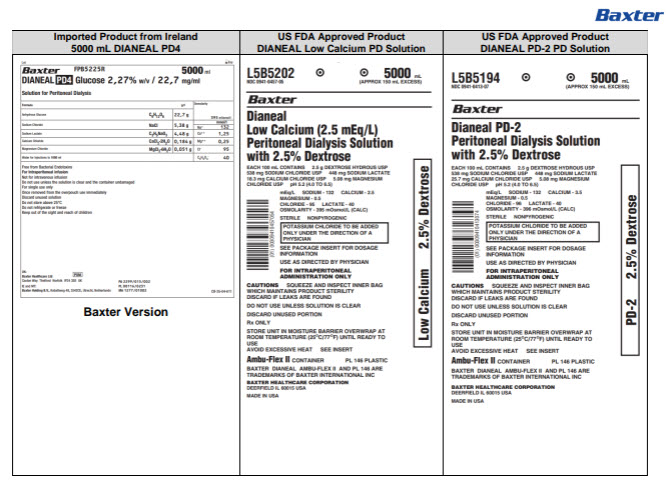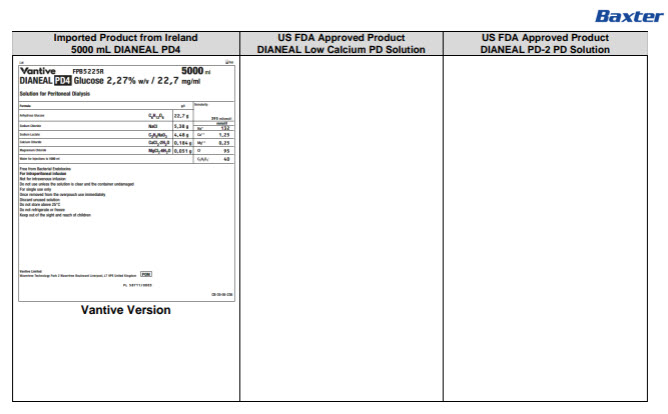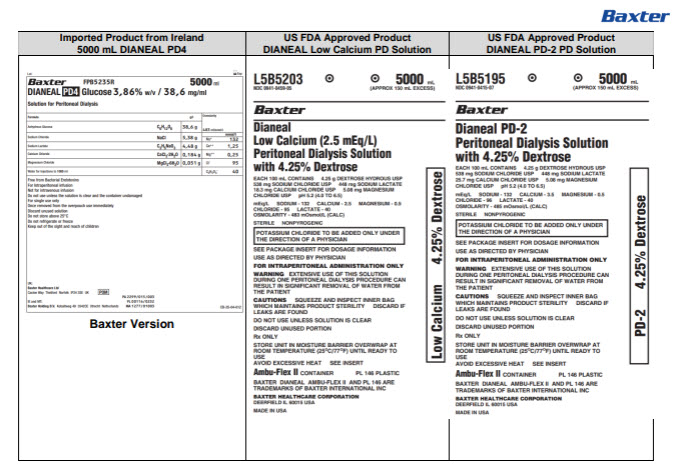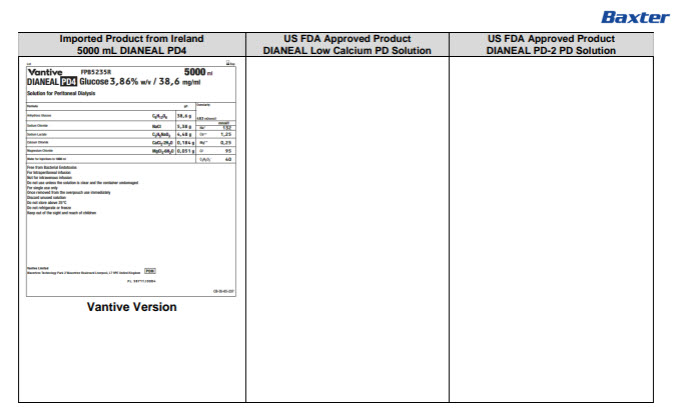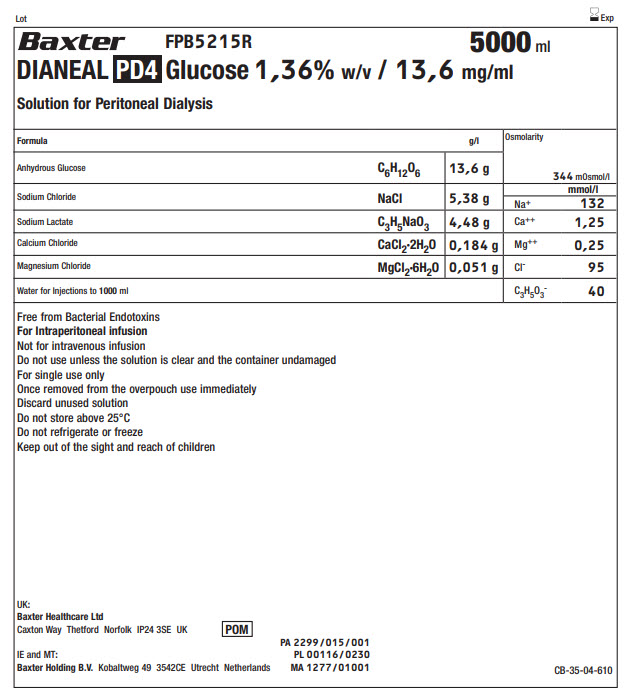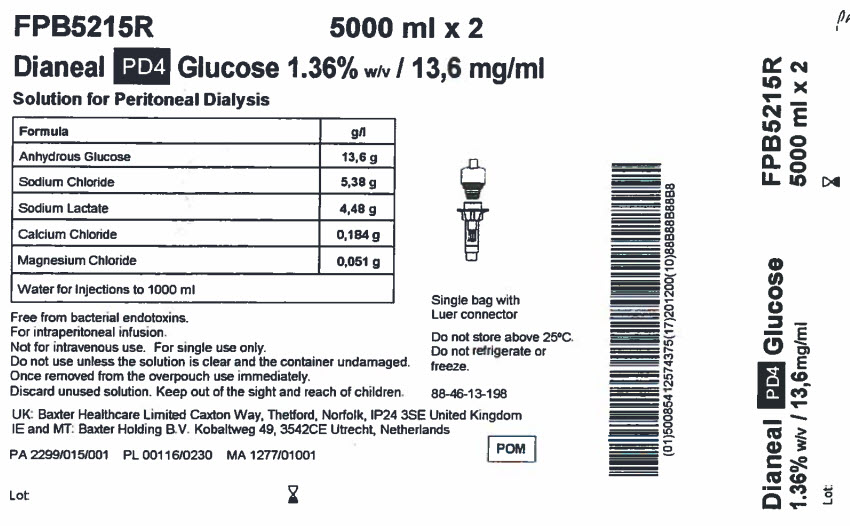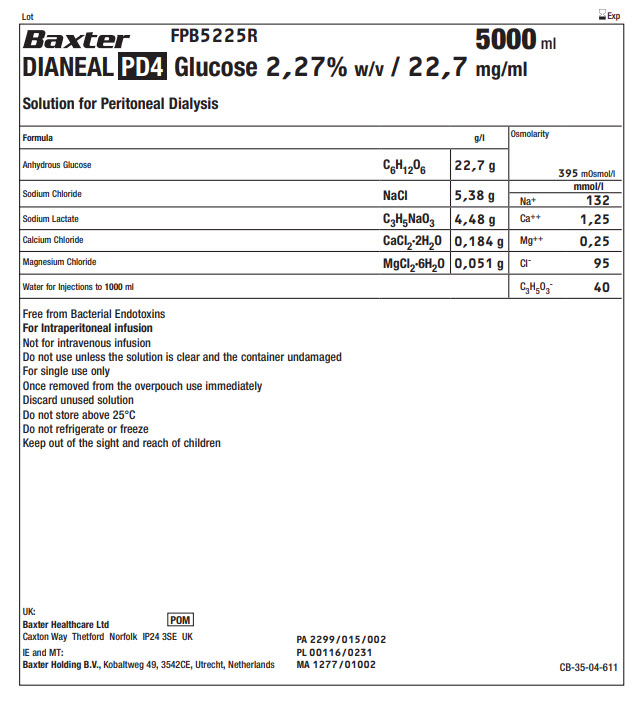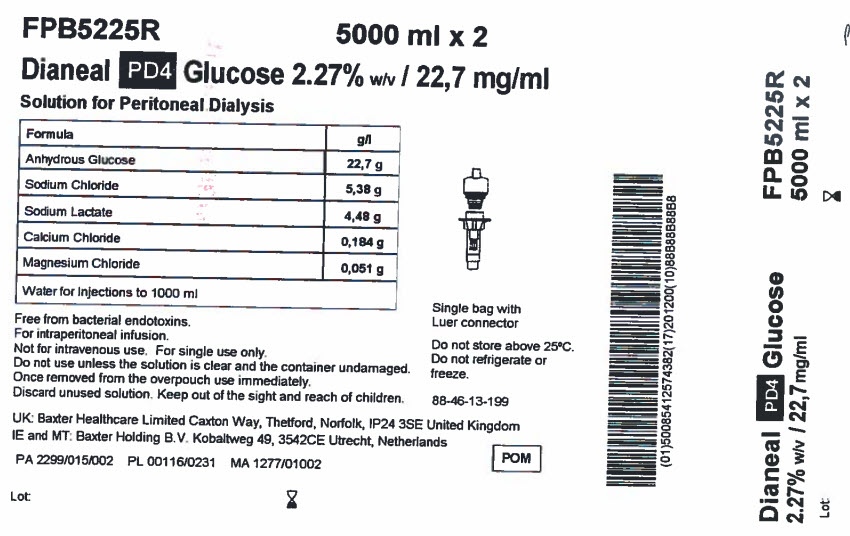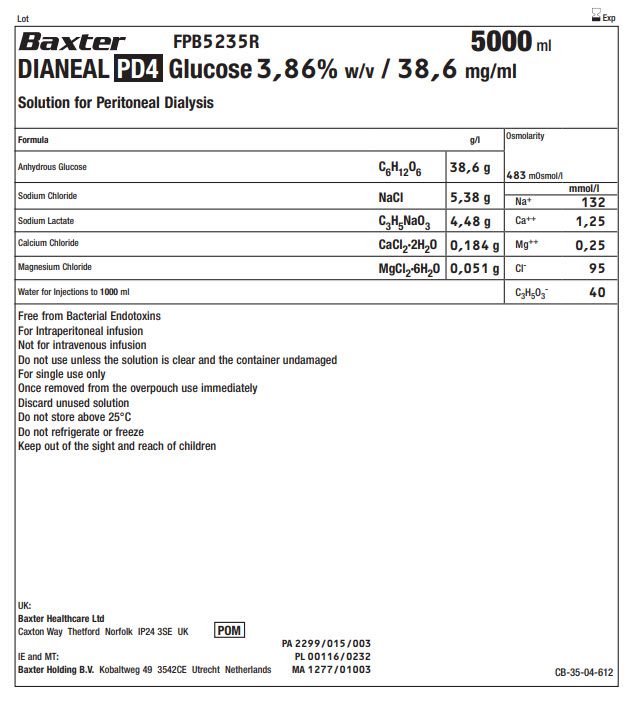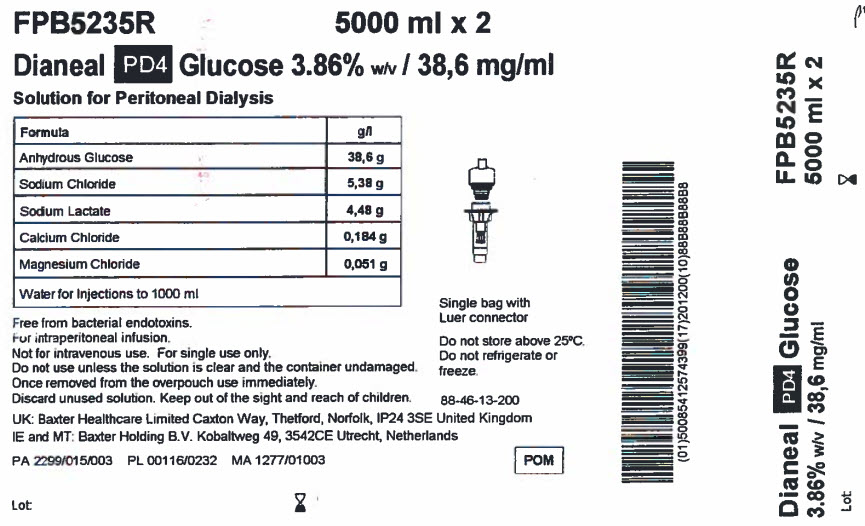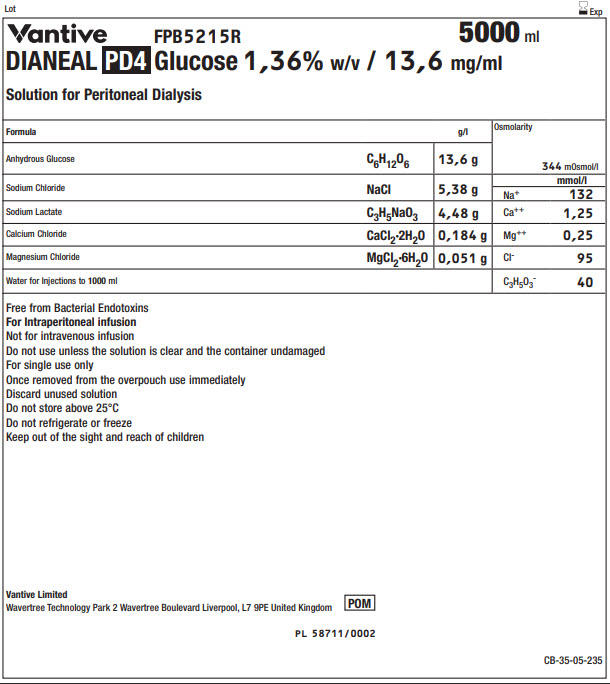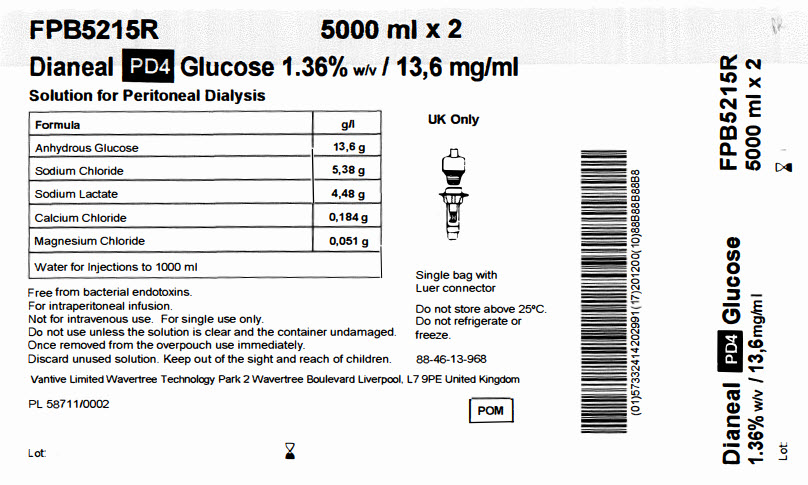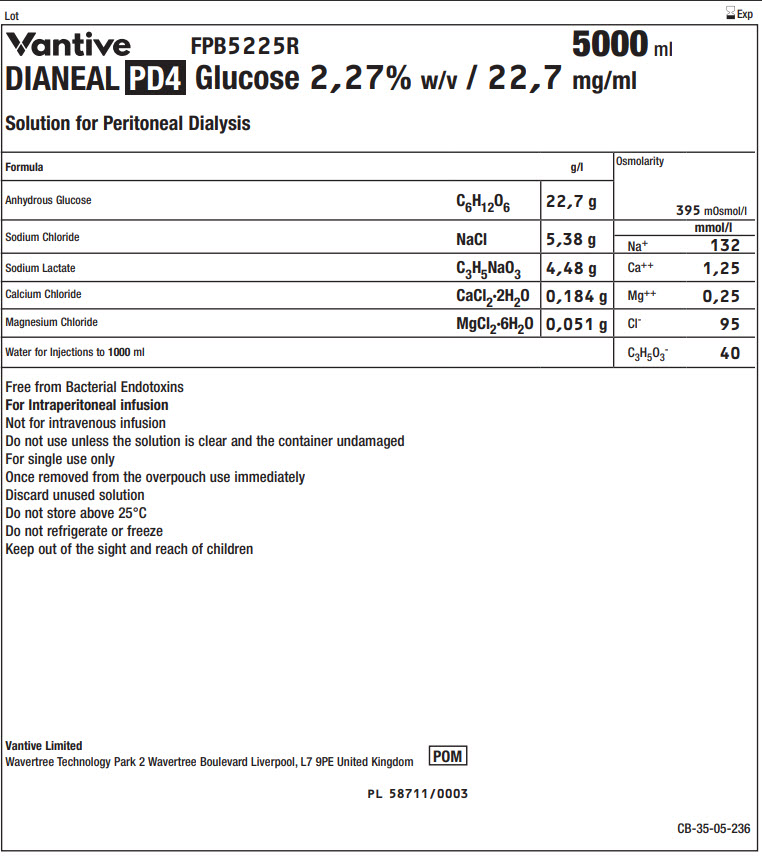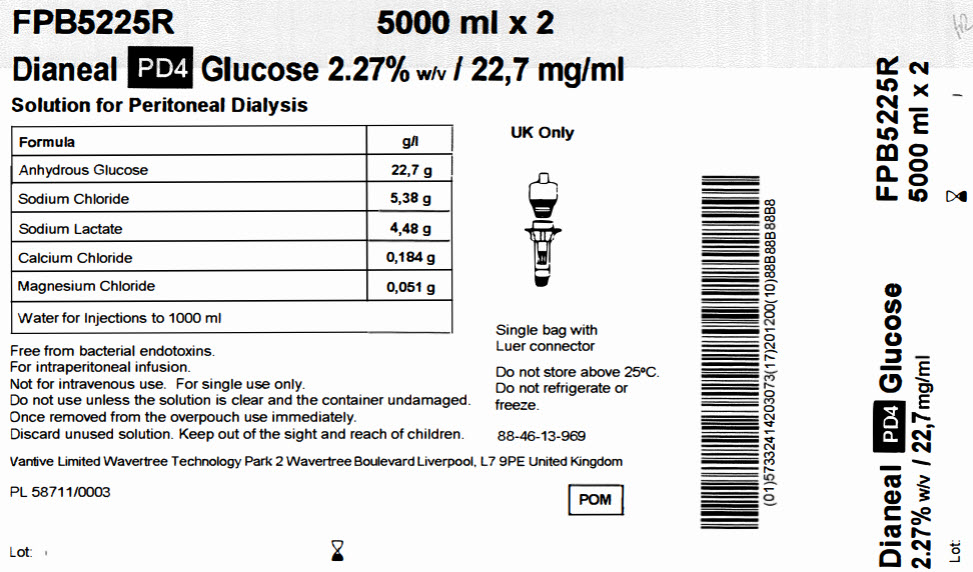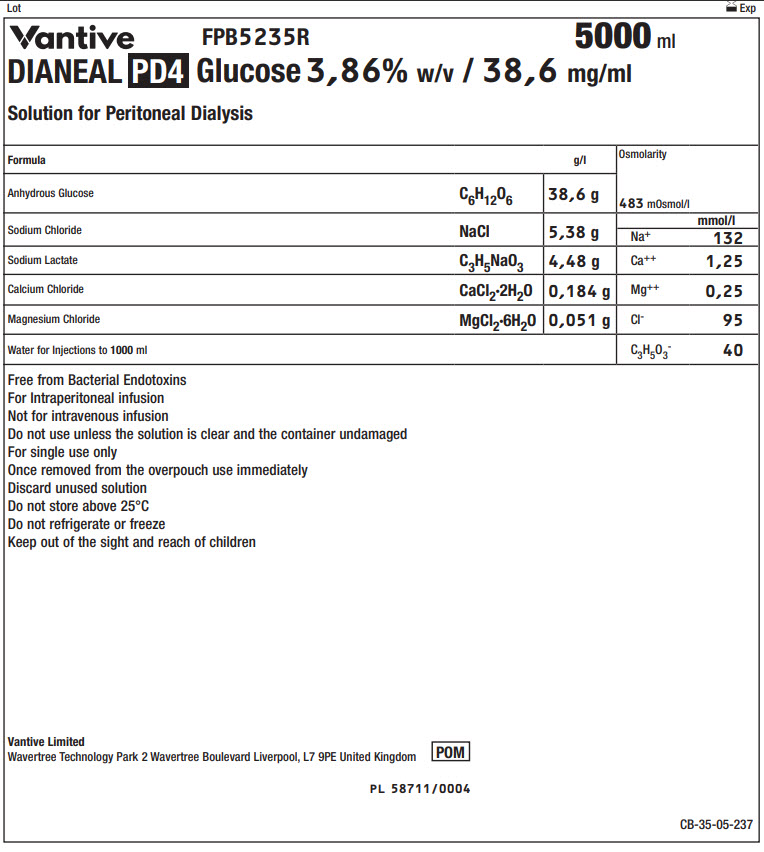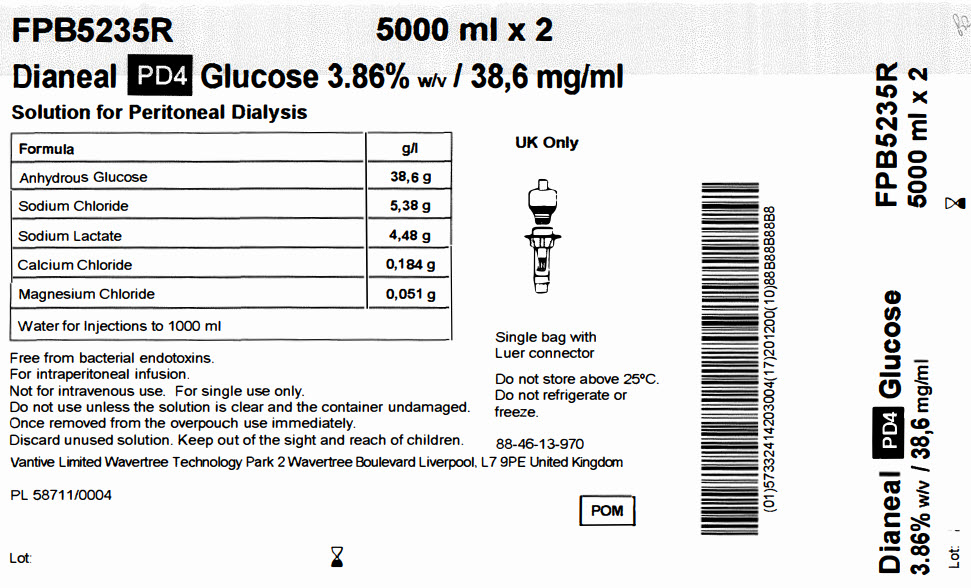 DRUG LABEL: DIANEAL LOW CALCIUM WITH DEXTROSE
NDC: 0941-0727 | Form: INJECTION, SOLUTION
Manufacturer: Vantive US Healthcare LLC
Category: prescription | Type: HUMAN PRESCRIPTION DRUG LABEL
Date: 20250702

ACTIVE INGREDIENTS: DEXTROSE MONOHYDRATE 1.5 g/100 mL; SODIUM CHLORIDE 538 mg/100 mL; SODIUM LACTATE 448 mg/100 mL; CALCIUM CHLORIDE 18.4 mg/100 mL; MAGNESIUM CHLORIDE 5.1 mg/100 mL
INACTIVE INGREDIENTS: WATER

DIANEAL Low Calcium with Dextrose

PACKAGE/LABEL PRINCIPAL DISPLAY PANEL

Lot Exp
BaxterLogo FPB5215R 5000 ml
DIANEAL PD4 Glucose 1,36% w/v / 13,6 mg/ml
Solution for Peritoneal Dialysis

Formula |  | g/l | Osmolarity | 344 mOsmol/l
Anhydrous Glucose | C6H12O6 | 13,6 g | Osmolarity | 344 mOsmol/l
Sodium Chloride | NaCl | 5,38 g | Na^+ | mmol/l
Sodium Chloride | NaCl | 5,38 g | Na^+ | 132
Sodium Lactate | C3H5NaO3 | 4,48 g | Ca^++ | 1,25
Calcium Chloride | CaCl2·2H2O | 0,184 g | Mg^++ | 0,25
Magnesium Chloride | MgCl2·6H2O | 0,051 g | Cl^- | 95
Water for Injections to 1000ml |  |  | C3H5O3^- | 40

Free from Bacterial Endotoxins
For Intraperitoneal infusion
Not for intravenous infusion
Do not use unless the solution is clear and the container undamaged
For single use only
Once removed from the overpouch use immediately
Discard unused solution
Do not store above 25°C
Do not refrigerate or freeze
Keep out of the sight and reach of children

UK:
Baxter Healthcare Ltd
Caxton Way Thetford Norfolk IP24 3SE UK

POM symbol

IE and MT:
Baxter Holding B.V.Kobaltweg 49 354CE Utrecht Netherlands

PA 2299/015/001
PL 00116/0230
MA 1277/01001

CB-35-04-610

FPB5215R 5000 ml x 2
Dianeal PD4 Glucose 1.36% w/v / 13,6 mg/ml
Solution for Peritoneal Dialysis

Formula | g/l
Anhydrous Glucose | 13,6 g
Sodium Chloride | 5,38 g
Sodium Lactate | 4,48 g
Calcium Chloride | 0,184 g
Magnesium Chloride | 0,051 g
Water for Injections to 1000 ml

Free from bacterial endotoxins.
For intraperitoneal infusion.
Not for intravenous use. For single use only.
Do not use unless the solution is clear and the container undamaged.
Once removed from the overpouch use immediately.
Discard unused solution. Keep out of the sight and reach of children.

UK: Baxter Healthcare Limited Caxton Way, Thetford, Norfolk, IP24 3SE United Kingdom
IE and MT: Baxter Holding B.V. Kobaltweg 49, 354CE Utrecht, Netherlands

PA 2299/015/001 PL 00116/0230 MA 1277/01001

Lot:

Single bag with
Luer connector

Do not store above 25°C.
Do not refrigerate or
freeze.

88-46-13-198

POM symbol

Barcode
(01)50085412574375(17)201200(10)88B88B88B8

Dianeal PD4 Glucose
1.36% w/v / 13,6mg/ml

Lot:

FPB5215R
5000 ml x 2

Lot Exp
BaxterLogo FPB5225R 5000 ml
DIANEAL PD4 Glucose 2,27% w/v / 22,7 mg/ml
Solution for Peritoneal Dialysis

Formula |  | g/l | Osmolarity | 395 mOsmol/l
Anhydrous Glucose | C6H12O6 | 22,7 g | Osmolarity | 395 mOsmol/l
Sodium Chloride | NaCl | 5,38 g | Na^+ | mmol/l
Sodium Chloride | NaCl | 5,38 g | Na^+ | 132
Sodium Lactate | C3H5NaO3 | 4,48 g | Ca^++ | 1,25
Calcium Chloride | CaCl2·2H2O | 0,184 g | Mg^++ | 0,25
Magnesium Chloride | MgCl2·6H2O | 0,051 g | Cl^- | 95
Water for Injections to 1000ml |  |  | C3H5O3^- | 40

Free from Bacterial Endotoxins
For Intraperitoneal infusion
Not for intravenous infusion
Do not use unless the solution is clear and the container undamaged
For single use only
Once removed from the overpouch use immediately
Discard unused solution
Do not store above 25°C
Do not refrigerate or freeze
Keep out of the sight and reach of children

UK:
Baxter Healthcare Ltd
Caxton Way Thetford Norfolk IP24 3SE UK

POM symbol

IE and MT:
Baxter Holding B.V.,Kobaltweg 49, 354CE, Utrecht, Netherlands

PA 2299/015/002
PL 00116/0231
MA 1277/01002

CB-35-04-611

FPB5225R 5000 ml x 2
Dianeal PD4 Glucose 2.27% w/v / 22,7 mg/ml
Solution for Peritoneal Dialysis

Formula | g/l
Anhydrous Glucose | 22,7 g
Sodium Chloride | 5,38 g
Sodium Lactate | 4,48 g
Calcium Chloride | 0,184 g
Magnesium Chloride | 0,051 g
Water for Injections to 1000 ml

Free from bacterial endotoxins.
For intraperitoneal infusion.
Not for intravenous use. For single use only.
Do not use unless the solution is clear and the container undamaged.
Once removed from the overpouch use immediately.
Discard unused solution. Keep out of the sight and reach of children.

UK: Baxter Healthcare Limited Caxton Way, Thetford, Norfolk, IP24 3SE United Kingdom
IE and MT: Baxter Holding B.V. Kobaltweg 49, 354CE Utrecht, Netherlands

PA 2299/015/002 PL 00116/0231 MA 1277/01002

Lot:

Single bag with
Luer connector

Do not store above 25°C.
Do not refrigerate or
freeze.

88-46-13-199

POM symbol

Barcode
(01)50085412574382(17)201200(10)88B88B88B8

Dianeal PD4 Glucose
2.27% w/v / 22,7mg/ml

Lot:

FPB5225R
5000 ml x 2

Lot Exp
BaxterLogo FPB5235R 5000 ml
DIANEAL PD4 Glucose 3,86% w/v / 38,6 mg/ml
Solution for Peritoneal Dialysis

Formula |  | g/l | Osmolarity | 395 mOsmol/l
Anhydrous Glucose | C6H12O6 | 38,6 g | Osmolarity | 395 mOsmol/l
Sodium Chloride | NaCl | 5,38 g | Na^+ | mmol/l
Sodium Chloride | NaCl | 5,38 g | Na^+ | 132
Sodium Lactate | C3H5NaO3 | 4,48 g | Ca^++ | 1,25
Calcium Chloride | CaCl2·2H2O | 0,184 g | Mg^++ | 0,25
Magnesium Chloride | MgCl2·6H2O | 0,051 g | Cl^- | 95
Water for Injections to 1000ml |  |  | C3H5O3^- | 40

Free from Bacterial Endotoxins
For Intraperitoneal infusion
Not for intravenous infusion
Do not use unless the solution is clear and the container undamaged
For single use only
Once removed from the overpouch use immediately
Discard unused solution
Do not store above 25°C
Do not refrigerate or freeze
Keep out of the sight and reach of children

UK:
Baxter Healthcare Ltd
Caxton Way Thetford Norfolk IP24 3SE UK

POM symbol

IE and MT:
Baxter Holding B.V.Kobaltweg 49 354CE Utrecht Netherlands

PA 2299/015/003
PL 00116/0232
MA 1277/01003

CB-35-04-612

FPB5235R 5000 ml x 2
Dianeal PD4 Glucose 3.86% w/v / 38,6 mg/ml
Solution for Peritoneal Dialysis

Formula | g/l
Anhydrous Glucose | 38,6 g
Sodium Chloride | 5,38 g
Sodium Lactate | 4,48 g
Calcium Chloride | 0,184 g
Magnesium Chloride | 0,051 g
Water for Injections to 1000 ml

Free from bacterial endotoxins.
For intraperitoneal infusion.
Not for intravenous use. For single use only.
Do not use unless the solution is clear and the container undamaged.
Once removed from the overpouch use immediately.
Discard unused solution. Keep out of the sight and reach of children.

UK: Baxter Healthcare Limited Caxton Way, Thetford, Norfolk, IP24 3SE United Kingdom
IE and MT: Baxter Holding B.V. Kobaltweg 49, 354CE Utrecht, Netherlands

PA 2299/015/003 PL 00116/0232 MA 1277/01003

Lot:

Single bag with
Luer connector

Do not store above 25°C.
Do not refrigerate or
freeze.

88-46-13-200

POM symbol

Barcode
(01)50085412574399(17)201200(10)88B88B88B8

Dianeal PD4 Glucose
3.86% w/v / 38,6mg/ml

Lot:

FPB5235R
5000 ml x 2

Lot Exp
Vantive Logo FPB5215R 5000 ml
DIANEAL PD4 Glucose 1,36% w/v / 13,6 mg/ml
Solution for Peritoneal Dialysis

Formula |  | g/l | Osmolarity | 344 mOsmol/l
Anhydrous Glucose | C6H12O6 | 13,6 g | Osmolarity | 344 mOsmol/l
Sodium Chloride | NaCl | 5,38 g | Na^+ | mmol/l
Sodium Chloride | NaCl | 5,38 g | Na^+ | 132
Sodium Lactate | C3H5NaO3 | 4,48 g | Ca^++ | 1,25
Calcium Chloride | CaCl2·2H2O | 0,184 g | Mg^++ | 0,25
Magnesium Chloride | MgCl2·6H2O | 0,051 g | Cl^- | 95
Water for Injections to 1000ml |  |  | C3H5O3^- | 40

Free from Bacterial Endotoxins
For Intraperitoneal infusion
Not for intravenous infusion
Do not use unless the solution is clear and the container undamaged
For single use only
Once removed from the overpouch use immediately
Discard unused solution
Do not store above 25°C
Do not refrigerate or freeze
Keep out of the sight and reach of children

Vantive Limited
Wavertree Technology Park 2 Wavertree Boulevard Liverpool, L7 9PE United Kingdom

POM symbol

PL 58711/0002
CB-35-05-235

FPB5215R 5000 ml x 2
Dianeal PD4 Glucose 1.36% w/v / 13,6 mg/ml
Solution for Peritoneal Dialysis

Formula | g/l
Anhydrous Glucose | 13,6 g
Sodium Chloride | 5,38 g
Sodium Lactate | 4,48 g
Calcium Chloride | 0,184 g
Magnesium Chloride | 0,051 g
Water for Injections to 1000 ml

Free from bacterial endotoxins.
For intraperitoneal infusion.
Not for intravenous use. For single use only.
Do not use unless the solution is clear and the container undamaged.
Once removed from the overpouch use immediately.
Discard unused solution. Keep out of the sight and reach of children.

Vantive Limited Wavertree Technology Park 2 Wavertree Boulevard Liverpool, L7 9PE United Kingdom

PL 58711/0002

Lot:

Single bag with
Luer connector

Do not store above 25°C.
Do not refrigerate or
freeze.

88-46-13-968

POM symbol

Barcode
(01)57332414202991(17)201200(10)88B88B88B8

Dianeal PD4 Glucose
1.36% w/v / 13,6mg/ml

Lot:

FPB5215R
5000 ml x 2

Lot Exp
Vantive Logo FPB5225R 5000 ml
DIANEAL PD4 Glucose 2,27% w/v / 22,7 mg/ml
Solution for Peritoneal Dialysis

Formula |  | g/l | Osmolarity | 395 mOsmol/l
Anhydrous Glucose | C6H12O6 | 22,7 g | Osmolarity | 395 mOsmol/l
Sodium Chloride | NaCl | 5,38 g | Na^+ | mmol/l
Sodium Chloride | NaCl | 5,38 g | Na^+ | 132
Sodium Lactate | C3H5NaO3 | 4,48 g | Ca^++ | 1,25
Calcium Chloride | CaCl2·2H2O | 0,184 g | Mg^++ | 0,25
Magnesium Chloride | MgCl2·6H2O | 0,051 g | Cl^- | 95
Water for Injections to 1000ml |  |  | C3H5O3^- | 40

Free from Bacterial Endotoxins
For Intraperitoneal infusion
Not for intravenous infusion
Do not use unless the solution is clear and the container undamaged
For single use only
Once removed from the overpouch use immediately
Discard unused solution
Do not store above 25°C
Do not refrigerate or freeze
Keep out of the sight and reach of children

Vantive Limited
Wavertree Technology Park 2 Wavertree Boulevard Liverpool, L7 9PE United Kingdom

POM symbol

PL 58711/0003

CB-35-05-236

FPB5225R 5000 ml x 2
Dianeal PD4 Glucose 2.27% w/v / 22,7 mg/ml
Solution for Peritoneal Dialysis

Formula | g/l
Anhydrous Glucose | 22,7 g
Sodium Chloride | 5,38 g
Sodium Lactate | 4,48 g
Calcium Chloride | 0,184 g
Magnesium Chloride | 0,051 g
Water for Injections to 1000 ml

Free from bacterial endotoxins.
For intraperitoneal infusion.
Not for intravenous use. For single use only.
Do not use unless the solution is clear and the container undamaged.
Once removed from the overpouch use immediately.
Discard unused solution. Keep out of the sight and reach of children.

Vantive Limited Wavertree Technology Park 2 Wavertree Boulevard Liverpool, L7 9PE United Kingdom

PL 58744/0003

Lot:

Single bag with
Luer connector

Do not store above 25°C.
Do not refrigerate or
freeze.

88-46-13-969

POM symbol

Barcode
(01)57332414203073(17)201200(10)88B88B88B8

Dianeal PD4 Glucose
2.27% w/v / 22,7mg/ml

Lot:

FPB5225R
5000 ml x 2

Lot Exp
Vantive Logo FPB5235R 5000 ml
DIANEAL PD4 Glucose 3,86% w/v / 38,6 mg/ml
Solution for Peritoneal Dialysis

Formula |  | g/l | Osmolarity | 395 mOsmol/l
Anhydrous Glucose | C6H12O6 | 38,6 g | Osmolarity | 395 mOsmol/l
Sodium Chloride | NaCl | 5,38 g | Na^+ | mmol/l
Sodium Chloride | NaCl | 5,38 g | Na^+ | 132
Sodium Lactate | C3H5NaO3 | 4,48 g | Ca^++ | 1,25
Calcium Chloride | CaCl2·2H2O | 0,184 g | Mg^++ | 0,25
Magnesium Chloride | MgCl2·6H2O | 0,051 g | Cl^- | 95
Water for Injections to 1000ml |  |  | C3H5O3^- | 40

Free from Bacterial Endotoxins
For Intraperitoneal infusion
Not for intravenous infusion
Do not use unless the solution is clear and the container undamaged
For single use only
Once removed from the overpouch use immediately
Discard unused solution
Do not store above 25°C
Do not refrigerate or freeze
Keep out of the sight and reach of children

Vantive Limited
Wavertree Technology Park 2 Wavertree Boulevard Liverpool, L7 9PE United Kingdom

POM symbol

PL 58711/0004

CB-35-05-237

FPB5235R 5000 ml x 2
Dianeal PD4 Glucose 3.86% w/v / 38,6 mg/ml
Solution for Peritoneal Dialysis

Formula | g/l
Anhydrous Glucose | 38,6 g
Sodium Chloride | 5,38 g
Sodium Lactate | 4,48 g
Calcium Chloride | 0,184 g
Magnesium Chloride | 0,051 g
Water for Injections to 1000 ml

Free from bacterial endotoxins.
For intraperitoneal infusion.
Not for intravenous use. For single use only.
Do not use unless the solution is clear and the container undamaged.
Once removed from the overpouch use immediately.
Discard unused solution. Keep out of the sight and reach of children.

Vantive Limited Wavertree Technology Park 2 Wavertree Boulevard Liverpool, L7 9PE United Kingdom

PL 58711/0004

Lot:

Single bag with
Luer connector

Do not store above 25°C.
Do not refrigerate or
freeze.

88-46-13-970

POM symbol

Barcode
(01)57332414203004(17)201200(10)88B88B88B8

Dianeal PD4 Glucose
3.86% w/v / 38,6mg/ml

Lot:

FPB5235R
5000 ml x 2